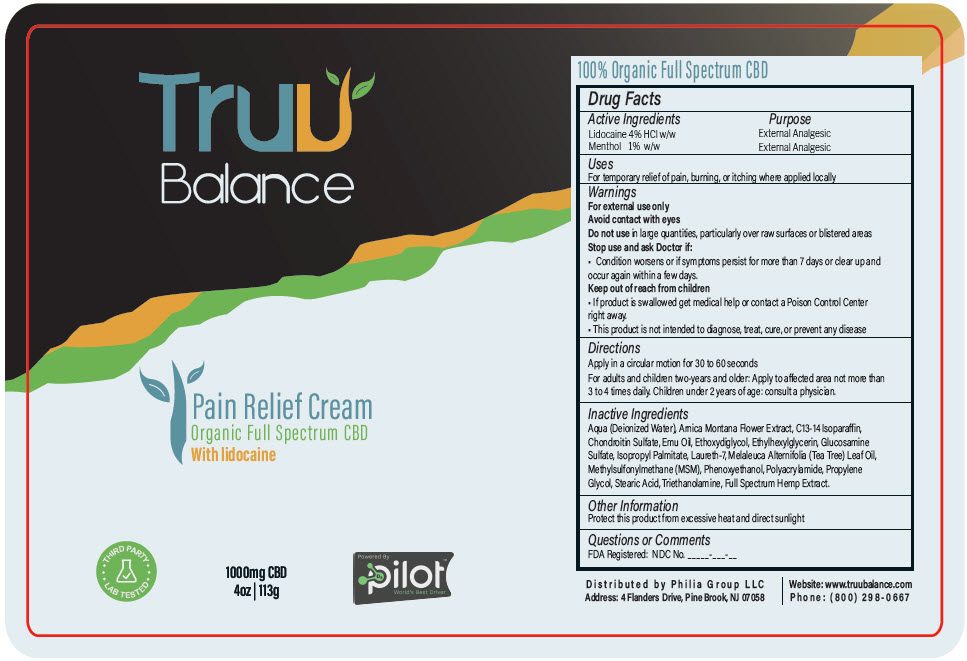 DRUG LABEL: Truu Balance Pain Relief
NDC: 73596-100 | Form: CREAM
Manufacturer: Philia Group LLC
Category: otc | Type: HUMAN OTC DRUG LABEL
Date: 20200813

ACTIVE INGREDIENTS: Lidocaine Hydrochloride 4000 mg/113 g; MENTHOL, UNSPECIFIED FORM 1000 mg/113 g
INACTIVE INGREDIENTS: WATER; ARNICA MONTANA FLOWER; C13-14 ISOPARAFFIN; EMU OIL; DIETHYLENE GLYCOL MONOETHYL ETHER; ETHYLHEXYLGLYCERIN; GLUCOSAMINE SULFATE; ISOPROPYL PALMITATE; LAURETH-7; TEA TREE OIL; DIMETHYL SULFONE; PHENOXYETHANOL; PROPYLENE GLYCOL; STEARIC ACID; TROLAMINE

Truu Balance Pain Relief

Drug Facts

ACTIVE INGREDIENT

Active Ingredients | Purpose
Lidocaine 4% HCl w/w | External Analgesic
Menthol 1% w/w | External Analgesic

Uses

For temporary relief of pain, burning, or itching where applied locally

Warnings

For eternal use only

Avoid contact with eyes

Do not use in large quantities, particularly over raw surfaces or blistered areas

Stop use and ask Doctor if

- Condition worsens or if symptoms persist for more than 7 days or clear up and occur again within a few days.

Keep out of reach of children

- If product is swallowed get medical help or contact a Poison Control Center right away.
- This product is not intended to diagnose, treat, cure or prevent any disease

Directions

Apply in a circular motion for 30 to 60 seconds

For adults and children two-years and older: apply to affected area not more than 3 to 4 times daily. Children under 2 years of age: consult a physician.

Inactive ingredients

Aqua (Deionized Water), Arnica Montana Flower Extract, C13-14 Isoparaffin, Chondroitin Sulfate, Emu Oil, Ethoxydiglycol, Ethylhexylglycerin, Glucosamine Sulfate, Isopropyl Palmitate, Laureth-7, Melaleuca Alternifolia (Tea Tree) Leaf Oil, Methylsulfonylmethane (MSM), Phenoxyethanol, Polyacrylamide, Propylene Glycol, Stearic Acid, Triethanolamine, Full Spectrum Hemp Extract. (Aerial Parts)

Other Information

Protect this product from excessive heat and direct sunlight

Questions or Comments

FDA Registered: NDC No. _____-___-__

Distributed by Philia Group LLC
Address: 4 Flanders Drive, Pine Brook, NJ 07058

PRINCIPAL DISPLAY PANEL - 113 g Bottle Label

Truu
Balance

Pain Relief Cream
Organic Full Spectrum CBD
With lidocaine

THIRD PARTY
LAB TESTED

1000mg CBD
4oz | 113g

Powered By
pilot™
World's Best Driver